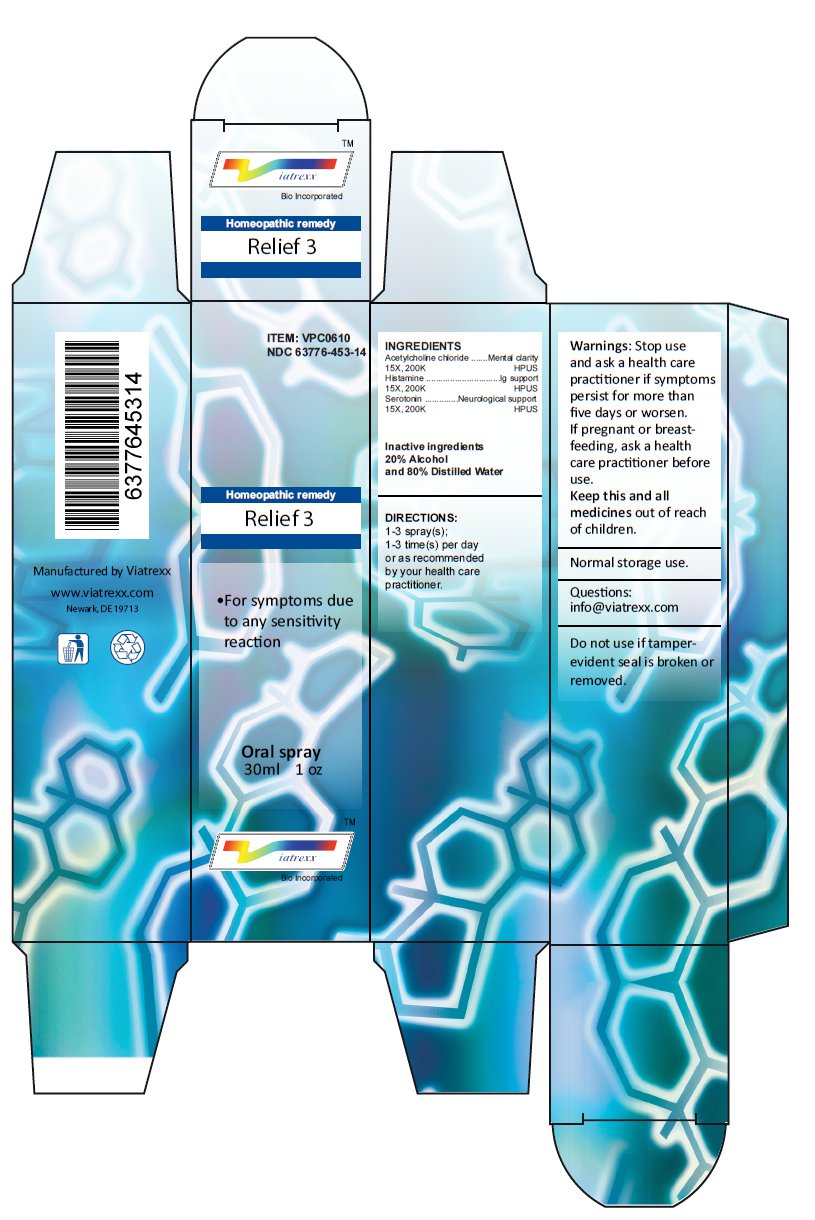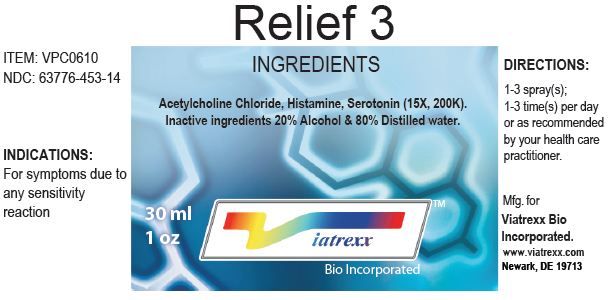 DRUG LABEL: Relief 3 
NDC: 63776-453 | Form: SPRAY
Manufacturer: VIATREXX BIO INCORPORATED
Category: homeopathic | Type: HUMAN OTC DRUG LABEL
Date: 20120724

ACTIVE INGREDIENTS: Acetylcholine Chloride 200 {kp_C}/1 mL; Histamine 200 {kp_C}/1 mL; Serotonin 200 {kp_C}/1 mL
INACTIVE INGREDIENTS: Alcohol; Water

Relief 3

Active Ingredients

Acetylcholine chloride 15X 200K, Histamine 15X 200K, Serotonin 15X 200K

Purpose:

Acetylcholine chloride | Mental clarity
Histamine | IG support
Serotonin | Neurological support

Uses

For symptoms due to any sensitivity reaction

Warnings

Stop use and ask a health care practitioner if symptoms persist for more than five days or worsen. If pregnant or breastfeeding, ask a health care practitioner before use.

Dosage

1-3 spray(s); 1-3 time(s) per day or as recommended by your health care practitioner.

KEEP OUT OF REACH OF CHILDREN

Keep this and all medicines out of reach of children.

Other Ingredients

Alcohol and Distilled Water

Other Information

Normal storage use.
Do not use if tamper-evident seal is broken or removed.

Questions

info@viatrexx.com

Principal Display Panel

ITEM: VPC0610
NDC 63776-453-14
Homeopathic remedy
Relief 3
• For symptons due to any sensitivity reaction
Oral spray
30ml 1 oz
Viatrexx™ Bio Incorporated
Manufactured by Viatrexx
www.viatrexx.com
Newark, DE 19713

Relief 3
30 mL
1 oz
Viatrexx™ Bio Incorporated
ITEM: VPC0610
NDC: 63776-453-14
INDICATIONS:
For symptoms due to any sensitivity reaction
DIRECTIONS:
1-3 spray(s); 1-3 time(s) per day or as recommended by your health care practitioner.
Mfg. for
Viatrexx Bio Incorporated.
www.viatrexx.com
Newark, DE 19713